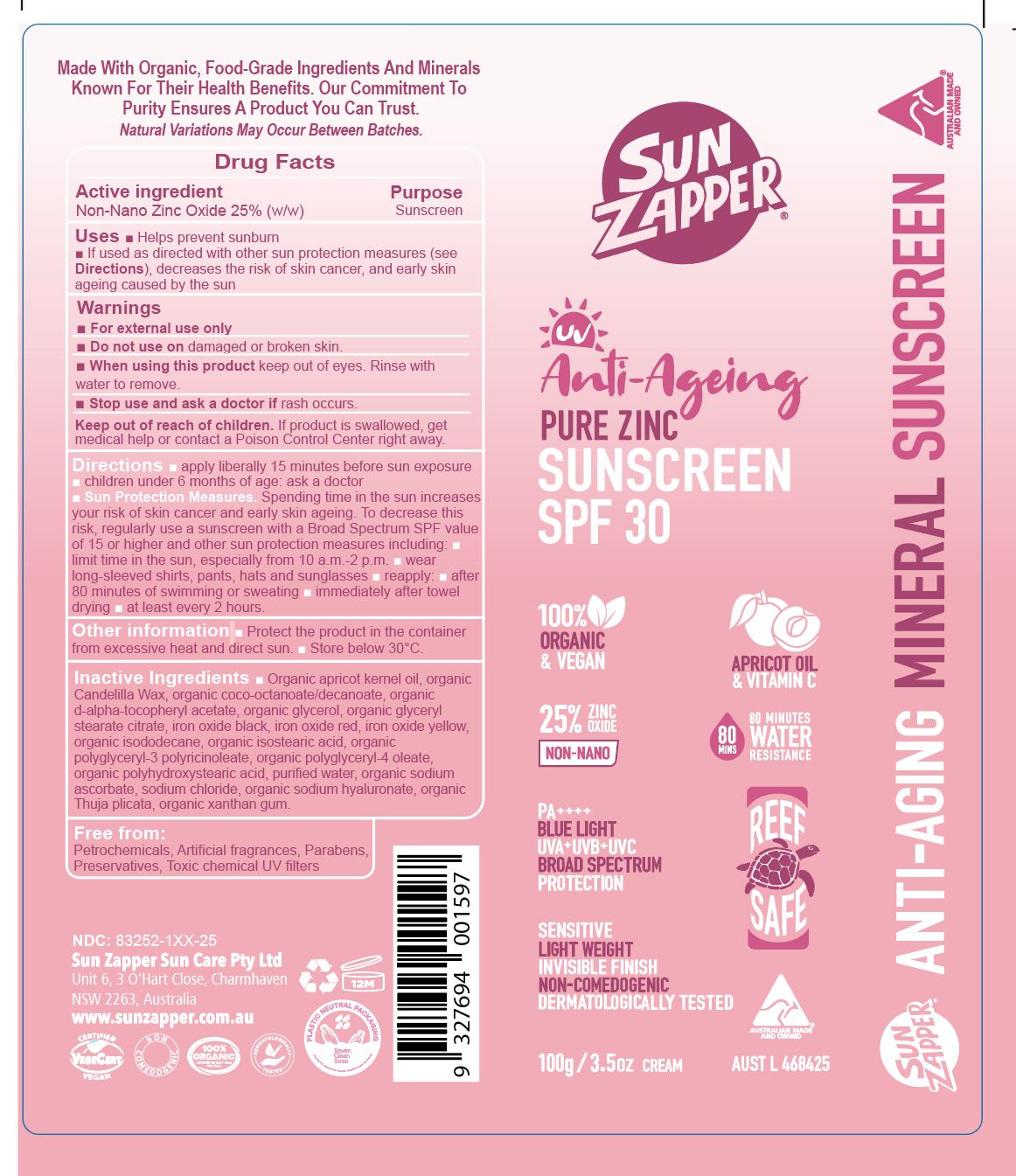 DRUG LABEL: Sun Zapper - Anti-ageing pure zinc sunscreen SPF30
NDC: 83252-128 | Form: CREAM
Manufacturer: VEGANIC SKN LIMITED
Category: otc | Type: HUMAN OTC DRUG LABEL
Date: 20250918

ACTIVE INGREDIENTS: ZINC OXIDE 25 kg/100 kg
INACTIVE INGREDIENTS: APRICOT SEED OIL; COCO-CAPRYLATE/CAPRATE; SODIUM CHLORIDE; GLYCERIN; POLYGLYCERYL-3 RICINOLEATE; GLYCERYL STEARATE CITRATE; XANTHAN GUM; FERRIC OXIDE RED; SODIUM HINOKITIOL; FERRIC OXIDE YELLOW; FERROSOFERRIC OXIDE; COCONUT ALKANES; ALPHA-TOCOPHEROL ACETATE; WATER; POLYHYDROXYSTEARIC ACID (2300 MW); ISOSTEARIC ACID; CANDELILLA WAX; SODIUM HYALURONATE; SODIUM ASCORBATE; POLYGLYCERYL-4 OLEATE

Sun Zapper - Anti-ageing pure zinc sunscreen SPF30

ACTIVE INGREDIENT

Zinc oxide - 25%

PURPOSE

Sunscreen

INDICATIONS AND USAGE

kindly refer to label picture

WARNINGS

For external use only.

Do not use on damaged r broken skin.

When using this product keep out of eyes. Rinse with water to remove.
Stop use and ask a doctor if rash occurs.

Keep out of reach of children.

If product is swallowed, get medical help or contact a Poison Control Center right away.

Keep out of reach of children.

DOSAGE AND ADMINISTRATION

Kindly refer to Label

INACTIVE INGREDIENT

See ingredients on label